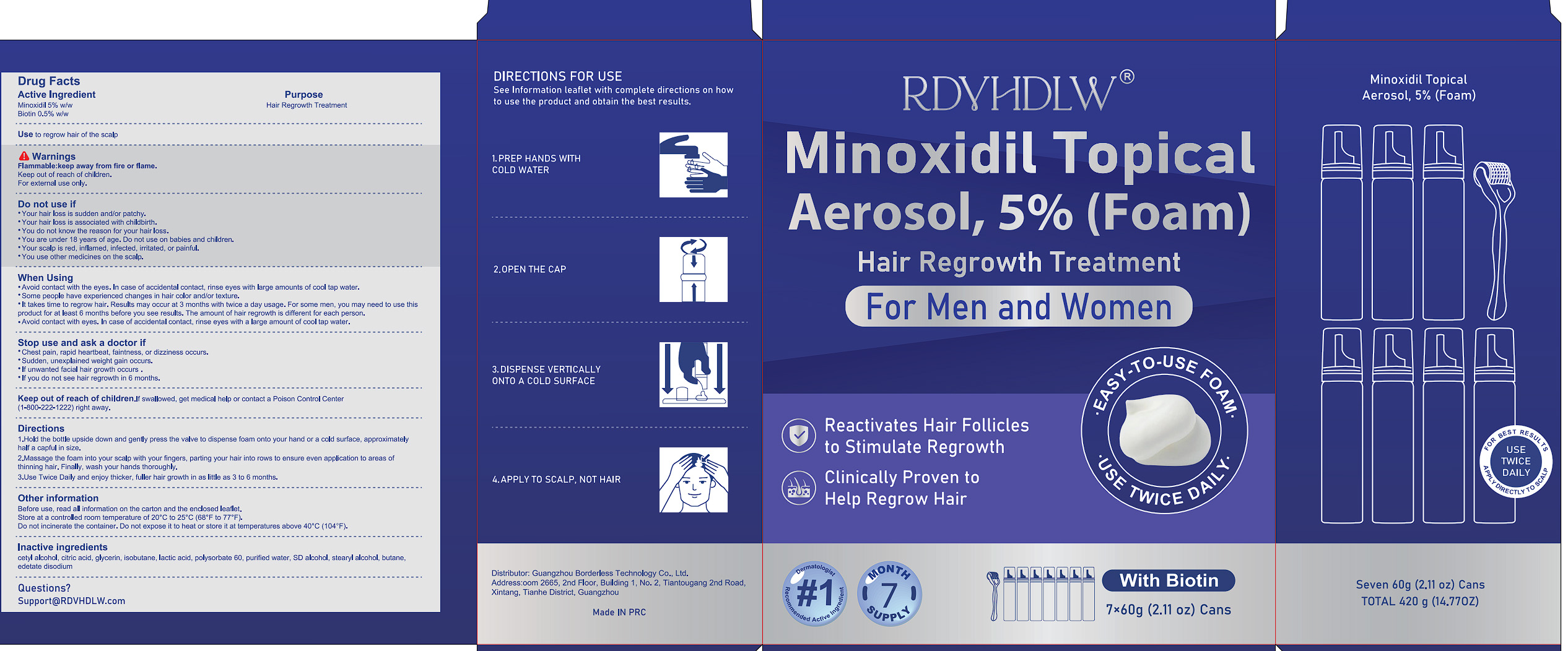 DRUG LABEL: RDVHDLW 5% Minoxidil Hair Growth Foam with Biotin
NDC: 85304-020 | Form: AEROSOL, FOAM
Manufacturer: Guangzhou Borderless Technology Co., Ltd.
Category: otc | Type: HUMAN OTC DRUG LABEL
Date: 20251022

ACTIVE INGREDIENTS: BIOTIN 0.5 g/100 g; MINOXIDIL 5 g/100 g
INACTIVE INGREDIENTS: WATER; EDETATE DISODIUM; CITRIC ACID; GLYCERIN; STEARYL ALCOHOL; BUTANE; CETYL ALCOHOL; ISOBUTANE; LACTIC ACID; ALCOHOL; POLYSORBATE 60

85304-020 RDVHDLW 5% Minoxidil Hair Growth Foam with Biotin

ACTIVE INGREDIENT

Minoxidil 5%
Biotin 0.5%

PURPOSE

Hair Regrowth Treatment

INDICATIONS AND USAGE

Use to regrow hair of the scalp

WARNINGS

Flammable:keep away from fire or flame.
Keep out of reach of children.
For external use only.

DO NOT USE

Your hair loss is sudden and'or patchy.
Your hair loss is associated with childbirth.
You do not know the reason for your hair loss.
You are under 18 years of age. Do not use on babies and children.
Your scalp is red, inflamed, infected, irritated, or painful.
You use other medicines on the scalp.

WHEN USING

Avoid contact with the eyes. In case of accidental contact, rinse eyes with large amounts of cool tap water.
Some people have experienced changes in hair color andlor texture.
It takes time to regrow hair. Results may occur at 3 months with twice a day usage. For some men, you may need to use this product for at least 6 months before you see results. The amount of hair regrowth is different for each person.
Avoid contact with eyes. In case of accidental contact, rinse eves with a large amount of cool tap water.

STOP USE

Chest pain, rapid heartbeat, faintness, or dizziness occurs.
Sudden. unexplained weight gain occurs.
lf unwanted facial hair growth occurs.
If you do not see hair regrowth in 6 months.

Keep out of reach of children.lf swallowed, get medical help or contact a Poison Control Center
(1-800-222-1222) right away.

DOSAGE AND ADMINISTRATION

1.Hold the botle upside down and genly press the valve to dispense foam onto your hand or a cold surface, approximately half a capful in size.
2.Massage the foam into your scalp with your fingers, parting your hair into rows to ensure even application to areas of thinning hair. Finally, wash your hands thoroughly.
3.Use Twice Daily and enjoy thicker, fuller hair growth in as little as 3 to 6 months.

INACTIVE INGREDIENT

cetyl alcohol
citric acid
glycerin
isobutane
lactic acid
polysorbate 60
purified water
SD alcohol 40-B
stearyl alcohol
butane
edetate disodium